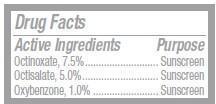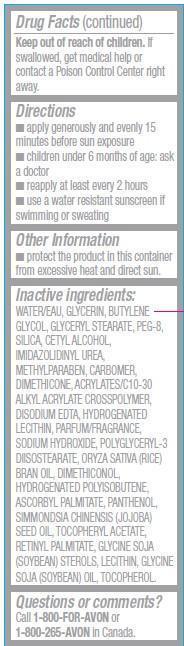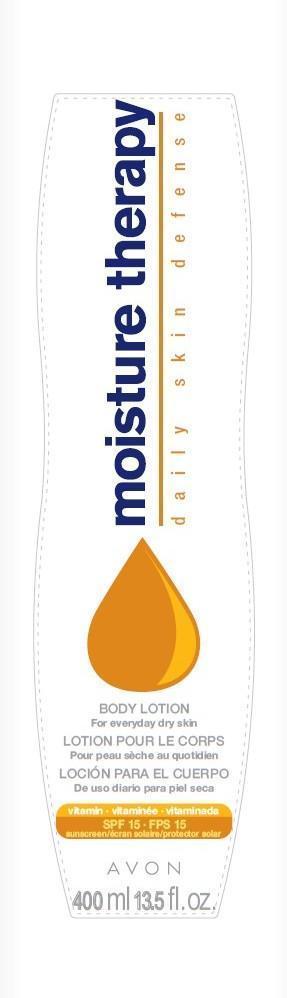 DRUG LABEL: Moisture Therapy
NDC: 10096-0291 | Form: LOTION
Manufacturer: Avon Products, Inc
Category: otc | Type: HUMAN OTC DRUG LABEL
Date: 20130227

ACTIVE INGREDIENTS: OCTINOXATE 75 mg/1 mL; OCTISALATE 50 mg/1 mL; OXYBENZONE 10 mg/1 mL

Active Ingredients
Octinoxate, 7.5%.............
Octisalate, 5.0%...............
Oxybenzone, 1.0% ..............

Purpose
............... Sunscreen
............... Sunscreen
.............. Sunscreen

Uses

- helps prevent sunburn

Warnings
Skin Cancer/Skin Aging Alert: Spending time in the sun increases your risk of skin cancer and early skin aging. This product has been shown only to help prevent sunburn, not skin cancer or early skin aging.
For external use only

Do not use on damaged or broken skin

When using this product keep out of eyes. Rinse with water to remove.

Stop use and ask a doctor if rash occurs

Keep out of reach of children. If swallowed, get medical help or contact a Poison Control Center right away.

Directions

- apply generously and evenly 15 minutes before sun exposure
- children under 6 month of age:ask a doctor
- reapply at least every 2 hours
- use a water resistant sunscreen if swimming or sweating

Other Information

- protect the product in this container from excessive heat and direct sun.

Inactive ingredients:
WATER/EAU, GLYCERIN, BUTYLENE GLYCOL, GLYCERYL STEARATE, PEG-8, SILICA, CETYL ALCOHOL, IMIDAZOLIDINYL UREA, METHYLPARABEN, CARBOMER, DIMETHICONE, ACRYLATES/C10-30 ALKYL ACRYLATE CROSSPOLYMER, DISODIUM EDTA, HYDROGENATED LECITHIN, PARFUM/FRAGRANCE, SODIUM HYDROXIDE, POLYGLYCERYL-3 DIISOSTEARATE, ORYZA SATIVA (RICE) BRAN OIL, DIMETHICONOL, HYDROGENATED POLYISOBUTENE, ASCORBYL PALMITATE, PANTHENOL, SIMMONDSIA CHINENSIS (JOJOBA) SEED OIL, TOCOPHERYL ACETATE,
RETINYL PALMITATE, GLYCINE SOJA (SOYBEAN) STEROLS, LECITHIN, GLYCINE SOJA (SOYBEAN) OIL, TOCOPHEROL.

Questions or comments?
Call 1-800-FOR-AVON or 1-800-265-AVON in Canada.